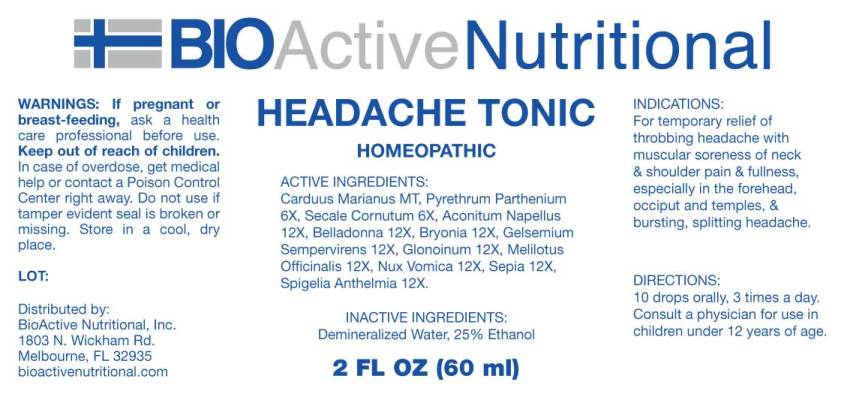 DRUG LABEL: Headache Tonic
NDC: 43857-0507 | Form: LIQUID
Manufacturer: BioActive Nutritional, Inc.
Category: homeopathic | Type: HUMAN OTC DRUG LABEL
Date: 20241017

ACTIVE INGREDIENTS: MILK THISTLE 1 [hp_X]/1 mL; TANACETUM PARTHENIUM WHOLE 6 [hp_X]/1 mL; CLAVICEPS PURPUREA SCLEROTIUM 6 [hp_X]/1 mL; ACONITUM NAPELLUS WHOLE 12 [hp_X]/1 mL; ATROPA BELLADONNA 12 [hp_X]/1 mL; BRYONIA ALBA ROOT 12 [hp_X]/1 mL; GELSEMIUM SEMPERVIRENS ROOT 12 [hp_X]/1 mL; NITROGLYCERIN 12 [hp_X]/1 mL; MELILOTUS OFFICINALIS TOP 12 [hp_X]/1 mL; STRYCHNOS NUX-VOMICA SEED 12 [hp_X]/1 mL; SEPIA OFFICINALIS JUICE 12 [hp_X]/1 mL; SPIGELIA ANTHELMIA WHOLE 12 [hp_X]/1 mL
INACTIVE INGREDIENTS: WATER; ALCOHOL

DRUG FACTS:

ACTIVE INGREDIENTS:

Carduus Marianus MT, Pyrethrum Parthenium 6X, Secale Cornutum 6X, Aconitum Napellus 12X, Belladonna 12X, Bryonia (Alba) 12X, Gelsemium Sempervirens 12X, Glonoinum 12X, Melilotus Officinalis 12X, Nux Vomica 12X, Sepia 12X, Spigelia Anthelmia 12X.

INDICATIONS:

For temporary relief of throbbing headache with muscular soreness of neck & shoulder pain & fullness, especially in the forehead, occiput and temples, & bursting, splitting headache.

WARNINGS:

If pregnant or breast-feeding, ask a health care professional before use.

Keep out of reach of children. In case of overdose, get medical help or contact a Poison Control Center right away.

Do not use if tamper evident seal is broken or missing.

Store in cool, dry place.

Keep out of reach of children. In case of overdose, get medical help or contact a Poison Control Center right away.

DIRECTIONS:

10 drops orally, 3 times a day. Consult a physician for use in children under 12 years of age.

INDICATIONS:

For temporary relief of throbbing headache with muscular soreness of neck & shoulder pain & fullness, especially in the forehead, occiput and temples, & bursting, splitting headache.

INACTIVE INGREDIENTS:

Demineralized Water, 25% Ethanol.

QUESTIONS:

Distributed by:
BioActive Nutritional, Inc.
1803 N. Wickham Rd.
Melbourne, FL 32935
bioactivenutritional.com

PACKAGE LABEL DISPLAY:

BIOActive Nutritional
HEADACHE TONIC
HOMEOPATHIC
2 FL OZ (60 ml)